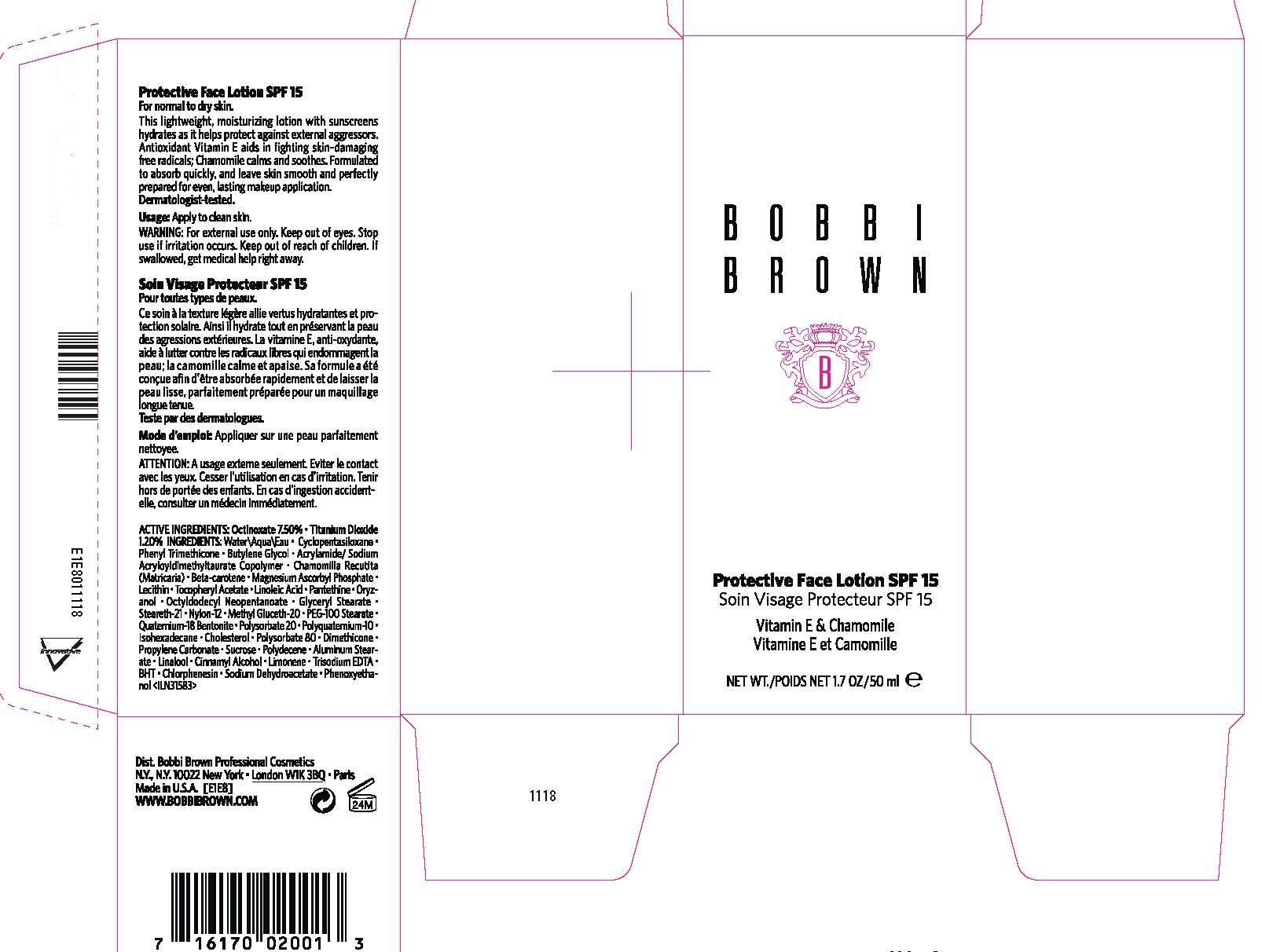 DRUG LABEL: BOBBI BROWN PROTECTIVE FACE 
NDC: 64141-866 | Form: LOTION
Manufacturer: Bobbi Brown Professional Cosmetics Inc.
Category: otc | Type: HUMAN OTC DRUG LABEL
Date: 20100713

ACTIVE INGREDIENTS: OCTINOXATE 7.5 mL/100 mL; TITANIUM DIOXIDE 1.2 mL/100 mL

ACTIVE INGREDIENT

ACTIVE INGREDIENTS: OCTINOXATE 7.50% [] TITANIUM DIOXIDE 1.20%

WHEN USING

USAGE: APPLY TO CLEAN SKIN

WARNINGS

WARNING: KEEP OUT OF EYES. STOP USE IF IRRITATION OCCURS. KEEP OUT OF REACH OF CHILDREN.

PACKAGE LABEL

BOBBI BROWN

PROTECTIVE FACE LOTION

SPF 15

1.7 FL. OZ/50 ML

DIST. BOBBI BROWN PROFESSIONAL COSMETICS

NEW YORK, NY 10022